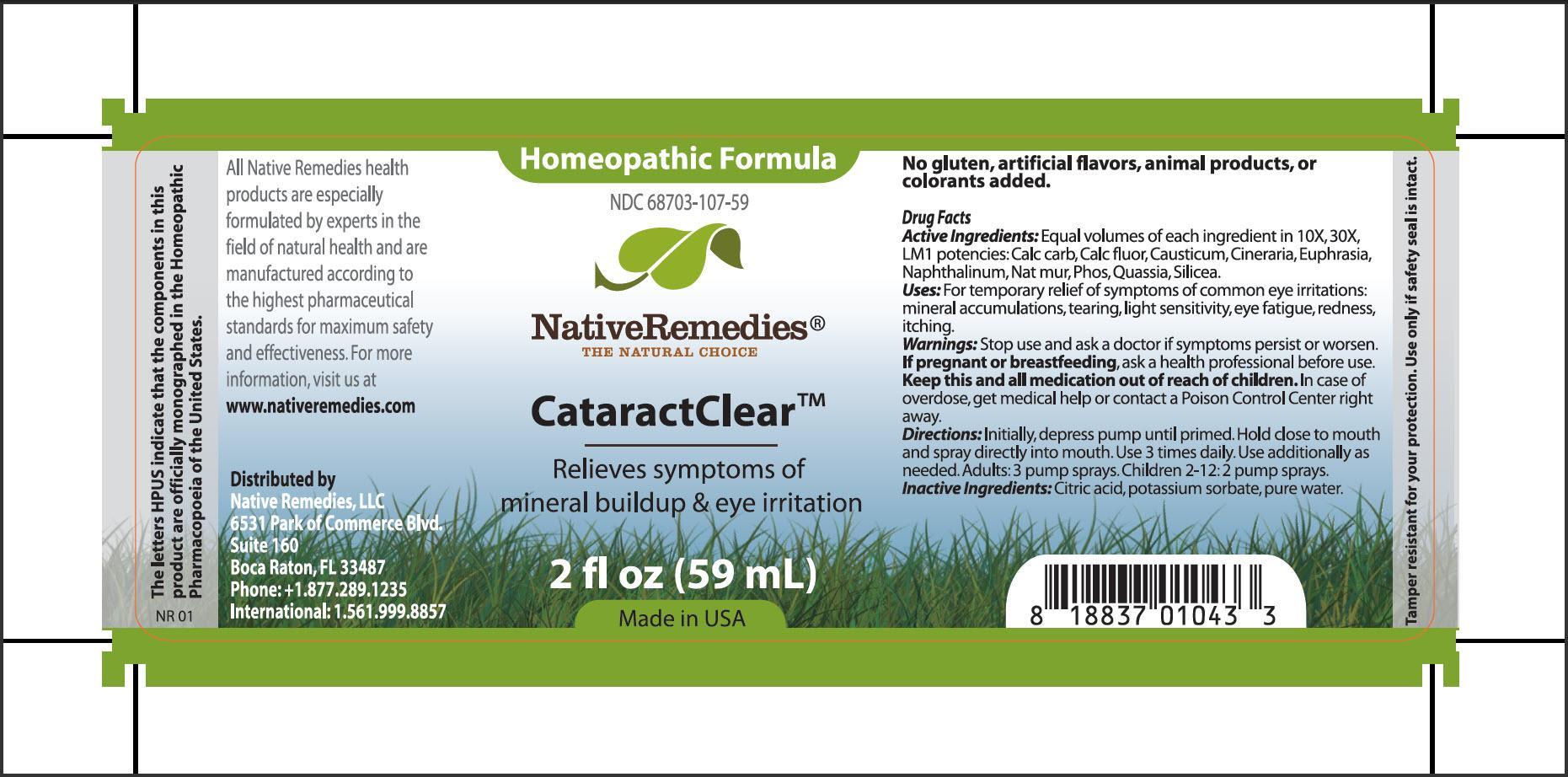 DRUG LABEL: CataractClear
NDC: 68703-107 | Form: SPRAY
Manufacturer: Native Remedies, LLC
Category: homeopathic | Type: HUMAN OTC DRUG LABEL
Date: 20130724

ACTIVE INGREDIENTS: OYSTER SHELL CALCIUM CARBONATE, CRUDE 10 [hp_X]/59 mL; CALCIUM FLUORIDE 10 [hp_X]/59 mL; CAUSTICUM 10 [hp_X]/59 mL; JACOBAEA MARITIMA 10 [hp_X]/59 mL; EUPHRASIA STRICTA 10 [hp_X]/59 mL; NAPHTHALENE 10 [hp_X]/59 mL; SODIUM CHLORIDE 10 [hp_X]/59 mL; PHOSPHORUS 10 [hp_X]/59 mL; QUASSIA AMARA WOOD 10 [hp_X]/59 mL; SILICON DIOXIDE 10 [hp_X]/59 mL
INACTIVE INGREDIENTS: CITRIC ACID MONOHYDRATE; POTASSIUM SORBATE; WATER

CataractClear

PURPOSE

Relieves symptoms of mineral buildup and eye irritation

Drug Facts
Active Ingredients: Equal volumes of each ingredient in 10X, 30X, LM1 potencies: Calc carb, Calc fluor, Casuticum, Cineraria, Euphrasia, Napthalinum, Nat mur, Phos, Quassia, Silicea

INDICATIONS AND USAGE

Uses: For temporary relief of symptoms of common eye irritations: mineral accumulations, tearing, light sensitivity, eye fatigue, redness, itching

WARNINGS

Warnings:Stop use and ask a doctor if symptoms persist or worsen

PREGNANCY OR BREAST FEEDING

If pregnant or breastfeeding, ask a health professional before use

KEEP OUT OF REACH OF CHILDREN

Keep this and all medication out of reach of children

OVERDOSAGE

In case of overdose, get medical help or contact a Poison Control Center right away

DOSAGE AND ADMINISTRATION

Directions:Initially, depress pump until primed. Hold close to mouth and spray directly into mouth. Use 3 times daily. Use additionally as needed. Adults: 3 pump sprays. Children 2-12: 2 pump sprays

Inactive Ingredients:Citric acid, potassium sorbate, pure water

PATIENT COUNSELING INFORMATION

The letters HPUS indicate that the components in this product are officially monographed in the Homeopathic Pharmacopoeia of the United States

All Native Remedies health product are especially formulated by experts in the field of natural health and are manufactured according to the highest pharmaceutical standards for maximum safety and effectiveness. For more information, visit us at www.nativeremedies.com

Distributed by
Native Remedies, LLC
6531 Park of Commerce Blvd.
Suite 160
Boca Raton, FL 33487
Phone: +1.877.289.1235
International: 1.561.999.8857

No gluten added, artificial flavors, animal products, or colorants added

STORAGE AND HANDLING

Tamper resistant for your protection. Use only if safety seal is intact